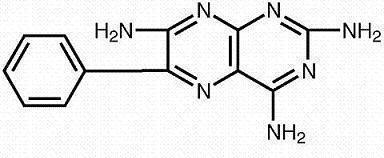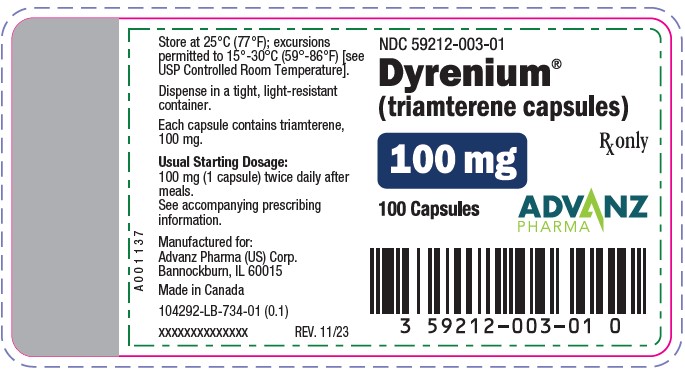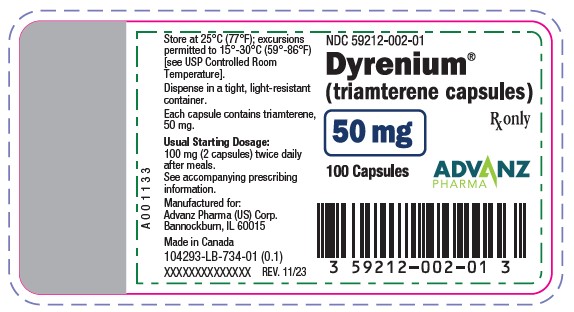 DRUG LABEL: Dyrenium
NDC: 59212-002 | Form: CAPSULE
Manufacturer: Advanz Pharma (US) Corp.
Category: prescription | Type: Human Prescription Drug Label
Date: 20241205

ACTIVE INGREDIENTS: TRIAMTERENE 50 mg/1 1
INACTIVE INGREDIENTS: D&C RED NO. 33; FD&C YELLOW NO. 6; GELATIN; LACTOSE; MAGNESIUM STEARATE; TITANIUM DIOXIDE

DYRENIUM® (triamterene USP) Capsules 50 mg and 100 mg potassium-sparing diuretic

Warnings

Abnormal elevation of serum potassium levels (greater than or equal to 5.5 mEq/liter) can occur with all potassium-sparing agents, including Dyrenium. Hyperkalemia is more likely to occur in patients with renal impairment and diabetes (even without evidence of renal impairment), and in the elderly or severely ill. Since uncorrected hyperkalemia may be fatal, serum potassium levels must be monitored at frequent intervals especially in patients receiving Dyrenium, when dosages are changed or with any illness that may influence renal function.

DESCRIPTION

Each capsule for oral use, with opaque red cap and body, contains Triamterene USP, 50 or 100 mg, and is imprinted with the product name, DYRENIUM, strength (50 mg or 100 mg) and WPC 002 (for the 50-mg strength) and WPC 003 (for the 100-mg strength). Inactive ingredients consist of D&C Red No. 33, FD&C Yellow No. 6, Gelatin NF, Lactose NF, Magnesium Stearate NF, and Titanium Dioxide USP.

Triamterene is 2,4,7-triamino-6-phenyl-pteridine:

Its molecular weight is 253.27. At 50°C, triamterene is slightly soluble in water. It is soluble in dilute ammonia, dilute aqueous sodium hydroxide and dimethylformamide. It is sparingly soluble in methanol.

CLINICAL PHARMACOLOGY

Triamterene has a unique mode of action; it inhibits the reabsorption of sodium ions in exchange for potassium and hydrogen ions at that segment of the distal tubule under the control of adrenal mineralocorticoids (especially aldosterone). This activity is not directly related to aldosterone secretion or antagonism; it is a result of a direct effect on the renal tubule.

The fraction of filtered sodium reaching this distal tubular exchange site is relatively small, and the amount which is exchanged depends on the level of mineralocorticoid activity. Thus, the degree of natriuresis and diuresis produced by inhibition of the exchange mechanism is necessarily limited. Increasing the amount of available sodium and the level of mineralocorticoid activity by the use of more proximally acting diuretics will increase the degree of diuresis and potassium conservation.

Triamterene occasionally causes increases in serum potassium which can result in hyperkalemia. It does not produce alkalosis, because it does not cause excessive excretion of titratable acid and ammonium.

Triamterene has been shown to cross the placental barrier and appear in the cord blood of animals.

Pharmacokinetics

Onset of action is 2 to 4 hours after ingestion. In normal volunteers the mean peak serum levels were 30 ng/mL at 3 hours. The average percent of drug recovered in the urine (0 to 48 hours) was 21%. Triamterene is primarily metabolized to the sulfate conjugate of hydroxytriamterene. Both the plasma and urine levels of this metabolite greatly exceed triamterene levels. Triamterene is rapidly absorbed, with somewhat less than 50% of the oral dose reaching the urine. Most patients will respond to Dyrenium (triamterene) during the first day of treatment. Maximum therapeutic effect, however, may not be seen for several days. Duration of diuresis depends on several factors, especially renal function, but it generally tapers off 7 to 9 hours after administration.

INDICATIONS AND USAGE

Dyrenium (triamterene) is indicated in the treatment of edema associated with congestive heart failure, cirrhosis of the liver and the nephrotic syndrome; steroid-induced edema, idiopathic edema and edema due to secondary hyperaldosteronism.

Dyrenium may be used alone or with other diuretics, either for its added diuretic effect or its potassium-sparing potential. It also promotes increased diuresis when patients prove resistant or only partially responsive to thiazides or other diuretics because of secondary hyperaldosteronism.

Usage in Pregnancy. The routine use of diuretics in an otherwise healthy woman is inappropriate and exposes mother and fetus to unnecessary hazard. Diuretics do not prevent development of toxemia of pregnancy, and there is no satisfactory evidence that they are useful in the treatment of developed toxemia.

Edema during pregnancy may arise from pathological causes or from the physiologic and mechanical consequences of pregnancy. Diuretics are indicated in pregnancy (however, see PRECAUTIONS below) when edema is due to pathologic causes, just as they are in the absence of pregnancy. Dependent edema in pregnancy, resulting from restriction of venous return by the expanded uterus, is properly treated through elevation of the lower extremities and use of support hose; use of diuretics to lower intravascular volume in this case is illogical and unnecessary. There is hypervolemia during normal pregnancy which is harmful to neither the fetus nor the mother (in the absence of cardiovascular disease), but which is associated with edema, including generalized edema, in the majority of pregnant women. If this edema produces discomfort, increased recumbency will often provide relief. In rare instances, this edema may cause extreme discomfort which is not relieved by rest. In these cases, a short course of diuretics may provide relief and may be appropriate.

CONTRAINDICATIONS

Anuria. Severe or progressive kidney disease or dysfunction, with the possible exception of nephrosis. Severe hepatic disease. Hypersensitivity to the drug or any of its components.

Dyrenium (triamterene) should not be used in patients with pre-existing elevated serum potassium, as is sometimes seen in patients with impaired renal function or azotemia, or in patients who develop hyperkalemia while on the drug. Patients should not be placed on dietary potassium supplements, potassium salts or potassium-containing salt substitutes in conjunction with Dyrenium.

Dyrenium should not be given to patients receiving other potassium-sparing agents, such as spironolactone, amiloride hydrochloride, or other formulations containing triamterene. Two deaths have been reported in patients receiving concomitant spironolactone and Dyrenium or Dyazide®. Although dosage recommendations were exceeded in one case and in the other serum electrolytes were not properly monitored, these two drugs should not be given concomitantly.

WARNINGS

Abnormal elevation of serum potassium levels (greater than or equal to 5.5 mEq/liter) can occur with all potassium-sparing agents, including Dyrenium. Hyperkalemia is more likely to occur in patients with renal impairment and diabetes (even without evidence of renal impairment), and in the elderly or severely ill. Since uncorrected hyperkalemia may be fatal, serum potassium levels must be monitored at frequent intervals especially in patients receiving Dyrenium, when dosages are changed or with any illness that may influence renal function.

WARNINGS AND PRECAUTIONS

There have been isolated reports of hypersensitivity reactions; therefore, patients should be observed regularly for the possible occurrence of blood dyscrasias, liver damage or other idiosyncratic reactions.

Periodic BUN and serum potassium determinations should be made to check kidney function, especially in patients with suspected or confirmed renal insufficiency. It is particularly important to make serum potassium determinations in elderly or diabetic patients receiving the drug; these patients should be observed carefully for possible serum potassium increases.

If hyperkalemia is present or suspected, an electrocardiogram should be obtained. If the ECG shows no widening of the QRS or arrhythmia in the presence of hyperkalemia, it is usually sufficient to discontinue Dyrenium (triamterene) and any potassium supplementation, and substitute a thiazide alone. Sodium polystyrene sulfonate may be administered to enhance the excretion of excess potassium. The presence of a widened QRS complex or arrhythmia in association with hyperkalemia requires prompt additional therapy. For tachyarrhythmia, infuse 44 mEq of sodium bicarbonate or 10 mL of 10% calcium gluconate or calcium chloride over several minutes. For asystole, bradycardia or A-V block transvenous pacing is also recommended.

The effect of calcium and sodium bicarbonate is transient and repeated administration may be required. When indicated by the clinical situation, excess K+ may be removed by dialysis or oral or rectal administration of Sodium polystyrene sulfonate. Infusion of glucose and insulin has also been used to treat hyperkalemia.

PRECAUTIONS

General

Dyrenium (triamterene) tends to conserve potassium rather than to promote the excretion as do many diuretics and, occasionally, can cause increases in serum potassium which, in some instances, can result in hyperkalemia. In rare instances, hyperkalemia has been associated with cardiac irregularities.

Electrolyte imbalance often encountered in such diseases as congestive heart failure, renal disease or cirrhosis may be aggravated or caused independently by any effective diuretic agent including Dyrenium. The use of full doses of a diuretic when salt intake is restricted can result in a low-salt syndrome.

Triamterene can cause mild nitrogen retention, which is reversible upon withdrawal of the drug, and is seldom observed with intermittent (every-other-day) therapy.

Triamterene may cause a decreasing alkali reserve, with the possibility of metabolic acidosis.

By the very nature of their illness, cirrhotics with splenomegaly sometimes have marked variations in their blood. Since triamterene is a weak folic acid antagonist, it may contribute to the appearance of megaloblastosis in cases where folic acid stores have been depleted. Therefore, periodic blood studies in these patients are recommended. They should also be observed for exacerbations of underlying liver disease.

Triamterene has elevated uric acid, especially in persons predisposed to gouty arthritis.

Triamterene has been reported in renal stones in association with other calculus components. Dyrenium should be used with caution in patients with histories of renal stones.

Information for Patients

To help avoid stomach upset, it is recommended that the drug be taken after meals.

If a single daily dose is prescribed, it may be preferable to take it in the morning to minimize the effect of increased frequency of urination on nighttime sleep.

If a dose is missed, the patient should not take more than the prescribed dose at the next dosing interval.

Laboratory Tests

Hyperkalemia will rarely occur in patients with adequate urinary output, but it is a possibility if large doses are used for considerable periods of time. If hyperkalemia is observed, Dyrenium (triamterene) should be withdrawn. The normal adult range of serum potassium is 3.5 to 5.0 mEq per liter, with 4.5 mEq often being used for a reference point. Potassium levels persistently above 6 mEq per liter require careful observation and treatment. Normal potassium levels tend to be higher in neonates (7.7 mEq per liter) than in adults.

Serum potassium levels do not necessarily indicate true body potassium concentration. A rise in plasma pH may cause a decrease in plasma potassium concentration and an increase in the intracellular potassium concentration. Because Dyrenium conserves potassium, it has been theorized that in patients who have received intensive therapy or been given the drug for prolonged periods, a rebound kaliuresis could occur upon abrupt withdrawal. In such patients, withdrawal of Dyrenium should be gradual.

Drug Interactions

Caution should be used when lithium and diuretics are used concomitantly because diuretic-induced sodium loss may reduce the renal clearance of lithium and increase serum lithium levels with risk of lithium toxicity. Patients receiving such combined therapy should have serum lithium levels monitored closely and the lithium dosage adjusted if necessary.

A possible interaction resulting in acute renal failure has been reported in a few subjects when indomethacin, a nonsteroidal anti-inflammatory agent, was given with triamterene. Caution is advised in administering nonsteroidal anti-inflammatory agents with triamterene.

The effects of the following drugs may be potentiated when given together with triamterene: antihypertensive medication, other diuretics, preanesthetic and anesthetic agents, skeletal muscle relaxants (non-depolarizing).

Potassium-sparing agents should be used with caution in conjunction with angiotensin-converting enzyme (ACE) inhibitors due to an increased risk of hyperkalemia.

The following agents, given together with triamterene, may promote serum potassium accumulation and possibly result in hyperkalemia because of the potassium-sparing nature of triamterene, especially in patients with renal insufficiency: blood from blood bank (may contain up to 30 mEq of potassium per liter of plasma or up to 65 mEq per liter of whole blood when stored for more than 10 days); low-salt milk (may contain up to 60 mEq of potassium per liter); potassium-containing medications (such as parenteral penicillin G potassium); salt substitutes (most contain substantial amounts of potassium).

Dyrenium (triamterene) may raise blood glucose levels; for adult-onset diabetes, dosage adjustments of hypoglycemic agents may be necessary during and/or after therapy; concurrent use with chlorpropamide may increase the risk of severe hyponatremia.

Drug/Laboratory Test Interactions

Triamterene and quinidine have similar fluorescence spectra;thus, triamterene will interfere with the fluorescent measurement of quinidine.

Carcinogenesis, Mutagenesis, Impairment of Fertility

Carcinogenesis: In studies conducted under the auspices of the National Toxicology Program, groups of rats were fed diets containing 0, 150, 300 or 600 ppm of triamterene, and groups of mice were fed diets containing 0, 100, 200 or 400 ppm triamterene. Male and female rats exposed to the highest tested concentration received triamterene at about 25 and 30 mg/kg/day, respectively. Male and female mice exposed to the highest tested concentration received triamterene at about 45 and 60 mg/kg/day, respectively.

There was an increased incidence of hepatocellular neoplasia (primarily adenomas) in male and female mice at the highest dosage level. These doses represent 7.5X and 10X the Maximum Recommended Human Dose (MRHD) of 300 mg/kg/day (or 6 mg/kg/day based on a 50 kg patient) for male and female mice, respectively, when based on body weight and 0.7X and 0.9X the MRHD when based on body-surface area.

Although hepatocellular neoplasia (exclusively adenomas) in the rat study was limited to triamterene-exposed males, incidence was not dose dependent and there was no statistically significant difference from control incidence at any dose level.

Mutagenesis: Triamterene was not mutagenic in bacteria (Salmonella typhimurium strains TA98, TA100, TA1535 or TA1537) with or without metabolic activation. It did not induce chromosomal aberrations in Chinese hamster ovary (CHO) cells in vitro with or without metabolic activation, but it did induce sister chromatid exchanges in CHO cells in vitro with and without metabolic activation.

Impairment of Fertility: Studies of the effects of triamterene on animal reproductive function have not been conducted.

Pregnancy

Teratogenic Effects:

Reproduction studies have been performed in rats at doses as high as 20 times the Maximum Recommended Human Dose (MRHD) on the basis of body weight, and 6 times the MRHD on the basis of body-surface area, without evidence of harm to the fetus due to triamterene. Because animal reproduction studies are not always predictive of human response, this drug should be used during pregnancy only if clearly needed.

Nonteratogenic Effects:

Triamterene has been shown to cross the placental barrier and appear in cord blood. The use of triamterene in pregnant women requires that the anticipated benefits be weighed against possible hazards to the fetus. These possible hazards include adverse reactions which have occurred in the adult.

Nursing Mothers:

Triamterene has not been studied in nursing mothers. Triamterene appears in animal milk and is likely present in human milk. If use of the drug product is deemed essential, the patient should stop nursing.

Pediatric Use:

Safety and effectiveness in pediatricpatients have not been established.

ADVERSE REACTIONS

Adverse effects are listed in decreasing order of frequency; however, the most serious adverse effects are listed first, regardless of frequency. All adverse effects occur rarely (that is, 1 in 1000, or less).

Hypersensitivity: anaphylaxis, rash, photosensitivity.

Metabolic: hyperkalemia, hypokalemia.

Renal: azotemia, elevated BUN and creatinine, renal stones, acute interstitial nephritis (rare), acute renal failure (one case of irreversible renal failure has been reported).

Gastrointestinal: jaundice and/or liver enzyme abnormalities, nausea and vomiting, diarrhea.

Hematologic: thrombocytopenia, megaloblastic anemia.

Central Nervous System: weakness, fatigue, dizziness, headache, dry mouth.

To report SUSPECTED ADVERSE REACTIONS, contact Advanz Pharma (US) Corp. at 1-877-370-1142 or FDA at 1-800-FDA-1088 or www.fda.gov/medwatch.

OVERDOSAGE

In the event of overdosage, it can be theorized that electrolyte imbalance would be the major concern, with particular attention to possible hyperkalemia. Other symptoms that might be seen would be nausea and vomiting,other G.I. disturbances and weakness. It is conceivable that some hypotension could occur. As with an overdose of any drug, immediate evacuation of the stomach should be induced through emesis and gastric lavage. Careful evaluation of the electrolyte pattern and fluid balance should be made. There is no specific antidote.

Reversible acute renal failure following ingestion of 50 tablets of a product containing a combination of 50 mg triamterene and 25 mg hydrochlorothiazide has been reported.

The oral LD50 in mice is 380 mg/kg. The amount of drug in a single dose ordinarily associated with symptoms of overdose or likely to be life-threatening is not known. Although triamterene is 67% protein bound, there may be some benefit to dialysis in cases of overdosage.

DOSAGE AND ADMINISTRATION

Adult Dosage

Dosage should be titrated to the needs of the individual patient. When used alone, the usual starting dose is 100 mg twice daily after meals. When combined with another diuretic or antihypertensive agent, the total daily dosage of each agent should usually be lowered initially and then adjusted to the patient’s needs. The total daily dosage should not exceed 300 mg. Please refer to PRECAUTIONS−General.

When Dyrenium (triamterene) is added to other diuretic therapy or when patients are switched to Dyrenium from other diuretics, all potassium supplementation should be discontinued.

HOW SUPPLIED

Capsules: 50 mg in bottles of 100, and 100 mg in bottles of 100.

STORAGE

Store at 25°C (77°F); excursions permitted to 15°-30°C (59°-86°F) [See USP Controlled Room Temperature]. Dispense in a tight, light resistant container.

50 mg 100s: NDC 59212-002-01

100 mg 100s: NDC 59212-003-01

Manufactured for:
Advanz Pharma (US) Corp.
Bannockburn, IL 60015

DYRENIUM® is a registered trademark of Mercury Pharma Group Limited. Distributed by Advanz Pharma (US) Corp. under license.

Made in Canada

PRINCIPAL DISPLAY PANEL - DYRENIUM 50 MG

NDC 59212-002-01

Dyrenium®
(triamterene) capsules

50 mg Rx only
100 Capsules ADVANZ PHARMA

PRINCIPAL DISPLAY PANEL - DYRENIUM 100 MG

NDC 59212-003-01

Dyrenium®
(triamterene) capsules

100 mg Rx only

100 Capsules ADVANZ PHARMA